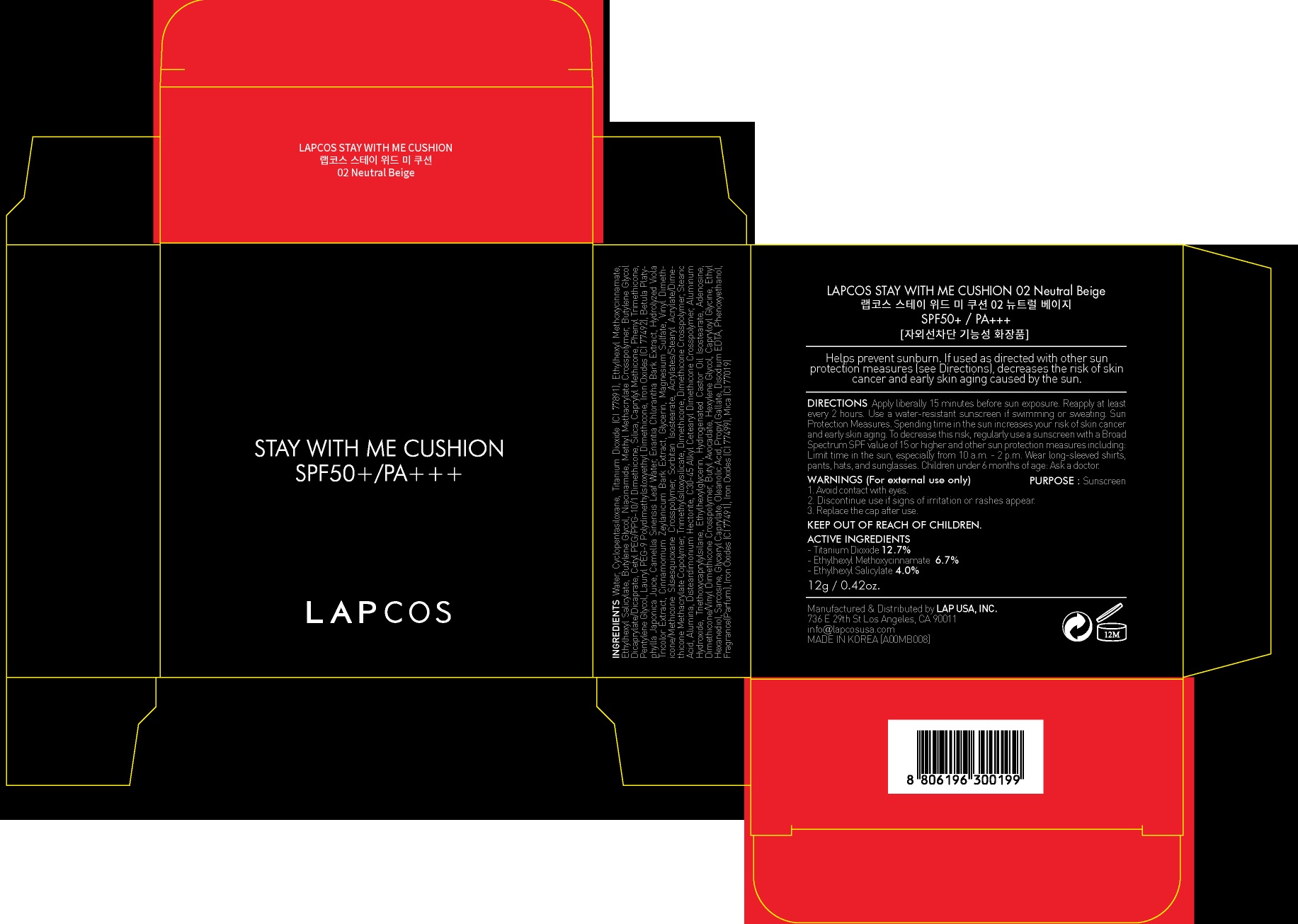 DRUG LABEL: LAPCOS Stay With Me Cushion 02 Neutral Beige
NDC: 71379-060 | Form: POWDER
Manufacturer: LAP CO.,LTD
Category: otc | Type: HUMAN OTC DRUG LABEL
Date: 20170504

ACTIVE INGREDIENTS: Titanium Dioxide 1.52 g/12 g; Octinoxate 0.80 g/12 g; Octisalate 0.48 g/12 g
INACTIVE INGREDIENTS: Water; Butylene Glycol

ACTIVE INGREDIENT

Active ingredients: Titanium Dioxide 12.7%, Ethylhexyl Methoxycinnamate 6.7%, Ethylhexyl Salicylate 4.0%

INACTIVE INGREDIENT

Inactive ingredients: Water, Cyclopentasiloxane, Butylene Glycol, Niacinamide, Methyl Methacrylate Crosspolymer, Butylene Glycol Dicaprylate/Dicaprate, Cetyl PEG/PPG-10/1 Dimethicone, Silica, Caprylyl Methicone, Phenyl Trimethicone, Pentylene Glycol, Lauryl PEG-9 Polydimethylsiloxyethyl Dimethicone, Iron Oxides (CI 77492), Betula Platyphylla Japonica Juice, Camellia Sinensis Leaf Water, Enantia Chlorantha Bark Extract, Hydrolyzed Viola Tricolor Extract, Cinnamomum Zeylanicum Bark Extract, Glycerin, Magnesium Sulfate, Vinyl Dimethicone/Methicone Silsesquioxane Crosspolymer, Sorbitan Isostearate, Acrylates/Stearyl Acrylate/Dimethicone Methacrylate Copolymer, Trimethylsiloxysilicate, Dimethicone, Dimethicone Crosspolymer, Stearic Acid, Alumina, Disteardimonium Hectorite, C30-45 Alkyl Cetearyl Dimethicone Crosspolymer, Aluminum Hydroxide, Triethoxycaprylylsilane, Ethylhexylglycerin, Hydrogenated Castor Oil Isostearate, Adenosine, Dimethicone/Vinyl Dimethicone Crosspolymer, Butyl Avocadate, Hexylene Glycol, Capryloyl Glycine, Ethyl Hexanediol, Sarcosine, Glyceryl Caprylate, Oleanolic Acid, Propyl Gallate, Disodium EDTA, Phenoxyethanol, Fragrance(Parfum), Iron Oxides (CI 77491), Iron Oxides (CI 77499), Mica (CI 77019)

PURPOSE

Purpose: Sunscreen

WARNINGS

Warnings: For external use only Avoid contact with eyes. Discontinue use if signs of irritation or rashes appear. Replace the cap after use. Keep Out of Reach of Children

DESCRIPTION

Uses: Helps prevent sunburn. If used as directed with other sun protection measures (see Directions), decreases the risk of skin cancer and early skin aging caused by the sun.

Directions: Apply liberally 15 minutes before sun exposure. Reapply at least every 2 hours. Use a water-resistant sunscreen if swimming or sweating. Sun Protection Measures. Spending time in the sun increases your risk of skin cancer and early skin aging. To decrease this risk, regularly use a sunscreen with a Broad Spectrum SPF value of 15 or higher and other sun protection measures including: Limit time in the sun, especially from 10 a.m. - 2 p.m. Wear long-sleeved shirts, pants, hats, and sunglasses. Children under 6 months of age: Ask a doctor.